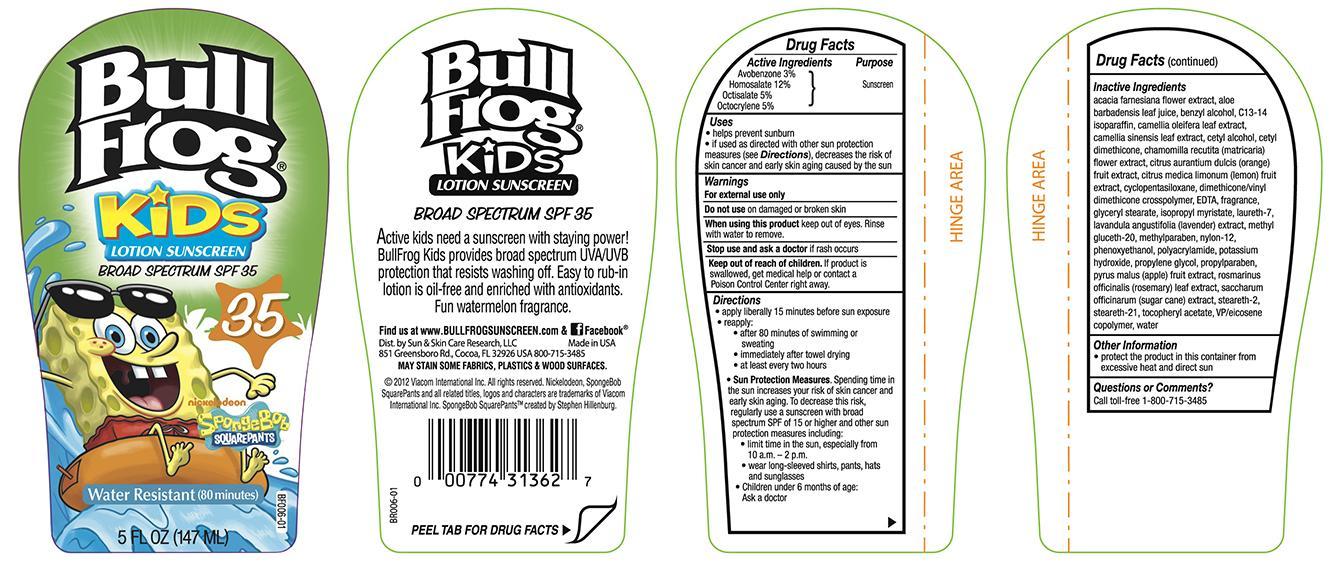 DRUG LABEL: Bull Frog Kids Sunscreen 35
NDC: 62802-362 | Form: LOTION
Manufacturer: Sun & Skin Care Research, LLC
Category: otc | Type: HUMAN OTC DRUG LABEL
Date: 20140325

ACTIVE INGREDIENTS: HOMOSALATE 12 g/100 g; OCTISALATE 5 g/100 g; AVOBENZONE 3 g/100 g; OCTOCRYLENE 5 g/100 g
INACTIVE INGREDIENTS: WATER; BENZYL ALCOHOL; CETYL ALCOHOL; CETYL DIMETHICONE 45; CYCLOMETHICONE 5; DIMETHICONE/VINYL DIMETHICONE CROSSPOLYMER (HARD PARTICLE); EDETATE DISODIUM; GLYCERYL STEARATE SE; METHYL GLUCETH-20; METHYLPARABEN; NYLON-12; PHENOXYETHANOL; OLEA EUROPAEA FRUIT VOLATILE OIL; POLYACRYLAMIDE (1500 MW); C13-14 ISOPARAFFIN; LAURETH-7; POTASSIUM HYDROXIDE; PROPYLPARABEN; STEARETH-2; ETHYLHEXYL PALMITATE; STEARETH-21; VITAMIN A PALMITATE; PVP/VA COPOLYMER; ALOE VERA LEAF

Drug Facts

Active Ingredients

Homosalate: 12%
Octisalate: 5%
Octocrylene: 5%
Avobenzone: 3%

Purpose

Sunscreen

Uses

- helps prevent sunburn
- If used as directed with other skin protection measures (see Directions), decreases the risk of skin cancer and early skin aging caused by the sun.

Warnings

For external use only. Do not use on damaged or broken skin. Stop use and ask a doctor if rash occurs. When using this product keep out of eyes. Rinse with water to remove. Keep out of the reach of children. If swallowed, get medical help or contact a Poison Control Center right away.

Directions

- apply liberally 15 minutes before sun exposure
- reapply after 80 minutes of swimming or sweating and immediately after towel drying
- at least every 2 hours
- Sun Protection Measures. Spending time in the sun increases your risk of skin cancer and early skin aging. To decrease this risk, regularly use a sunscreen with a Broad Spectrum SPF value of 15 or higher and other sun protection measures including limiting time in the sun, especially from 10a.m.-2p.m., wear long-sleeved shirts, pants, hats and sunglasses.
- children under 6 months: Ask a doctor

Other Information

- For use on skin only
- Avoid contact with fabric
- Protect this product from excessive heat and direct sun